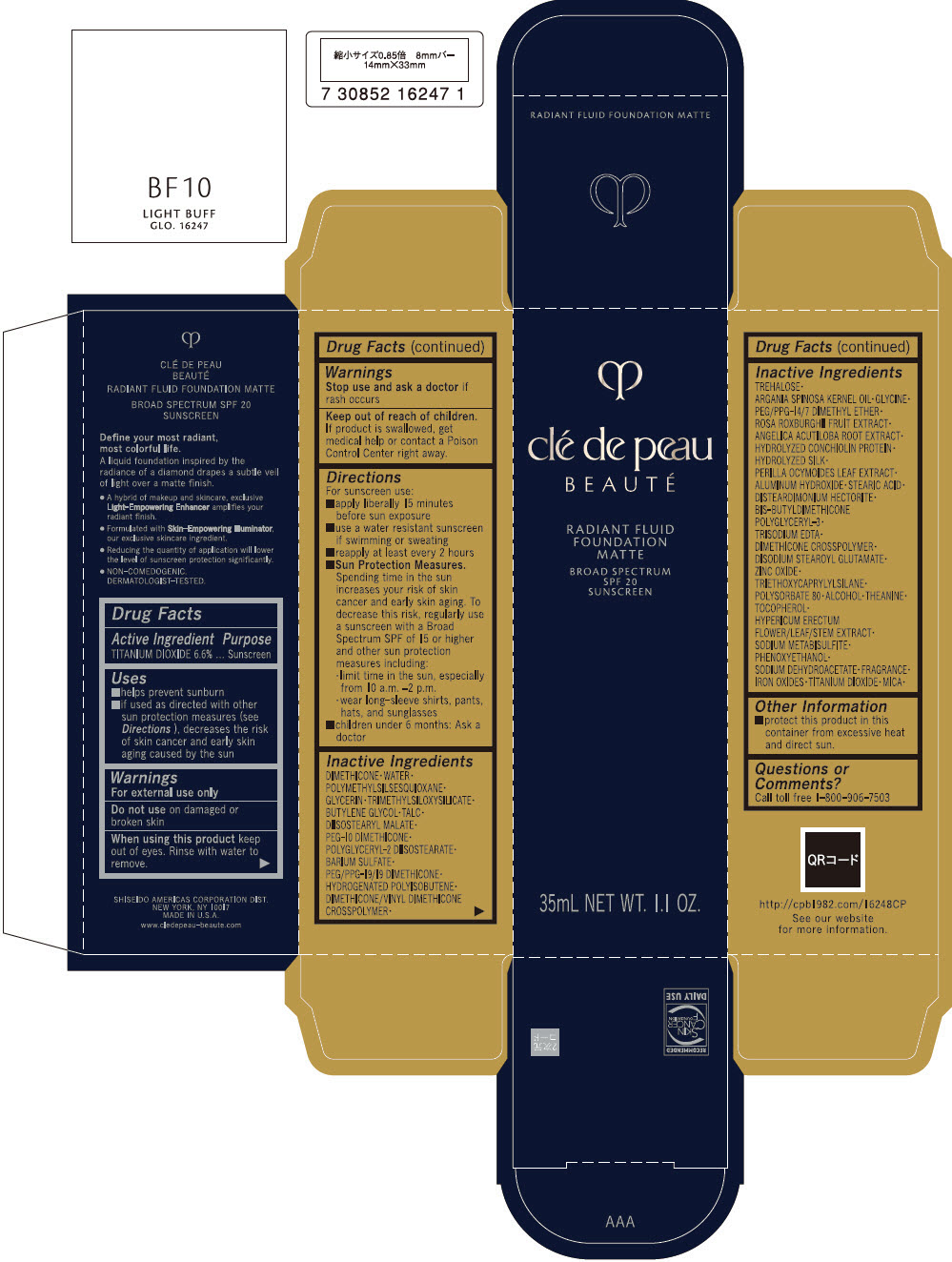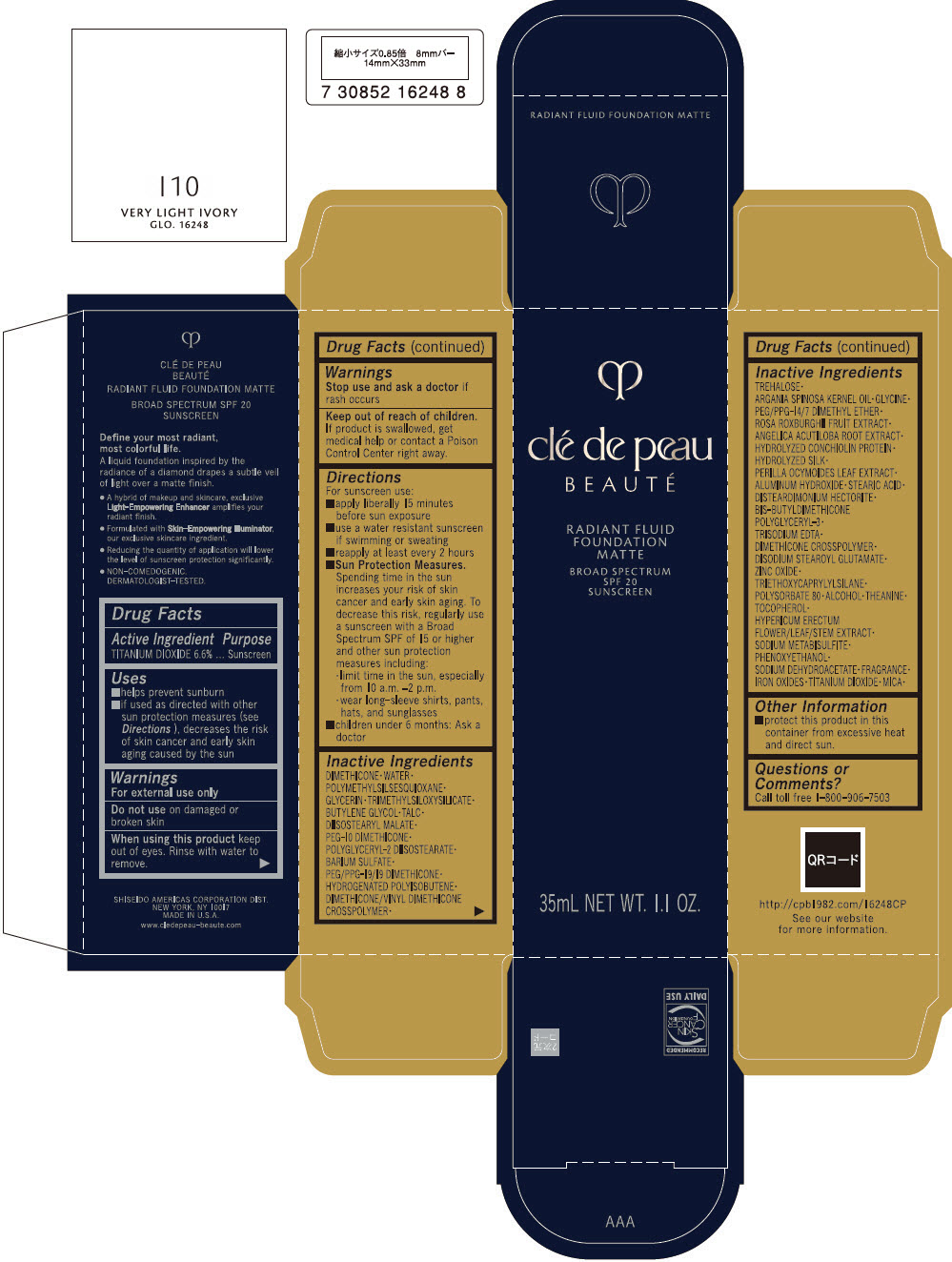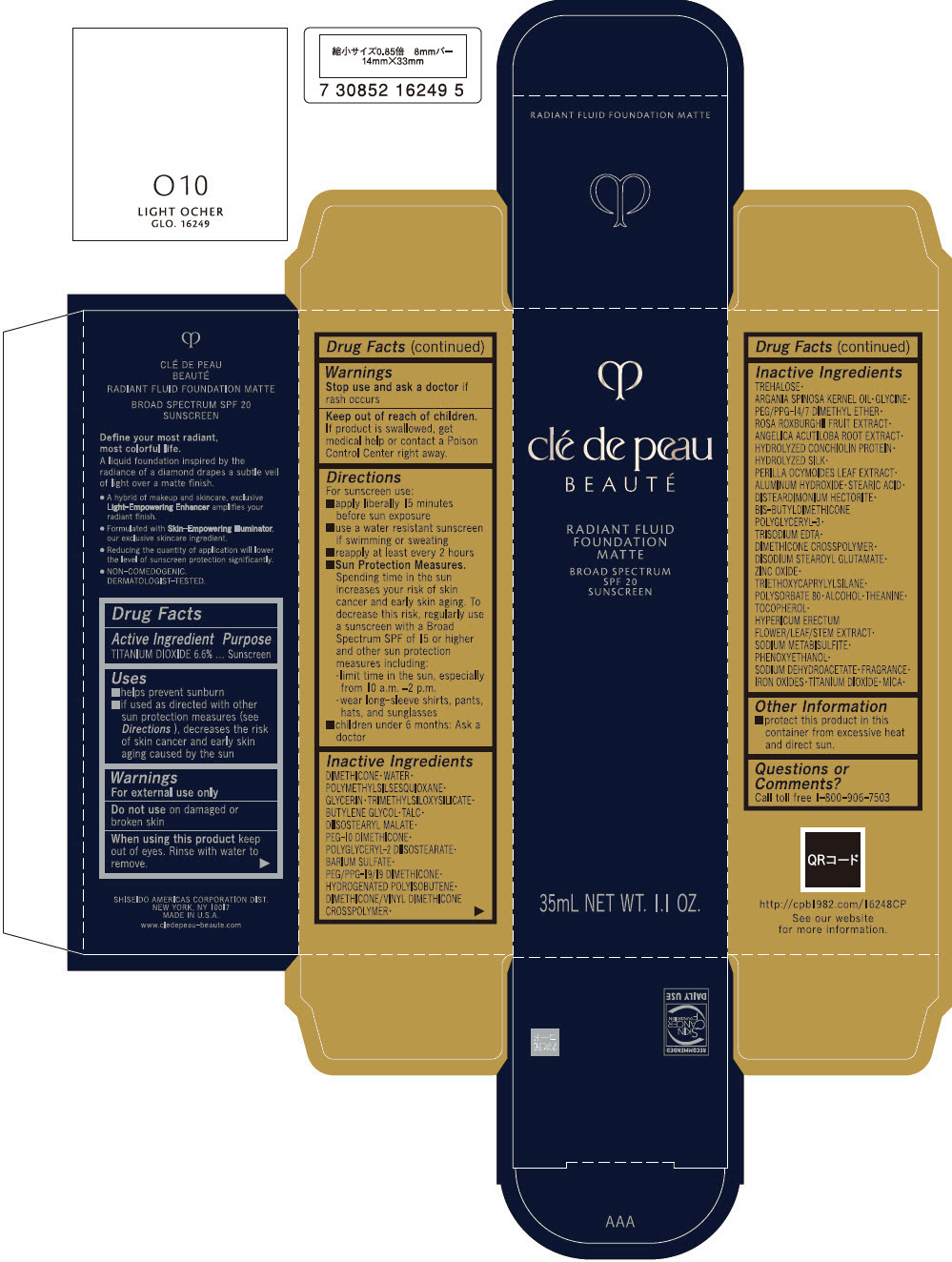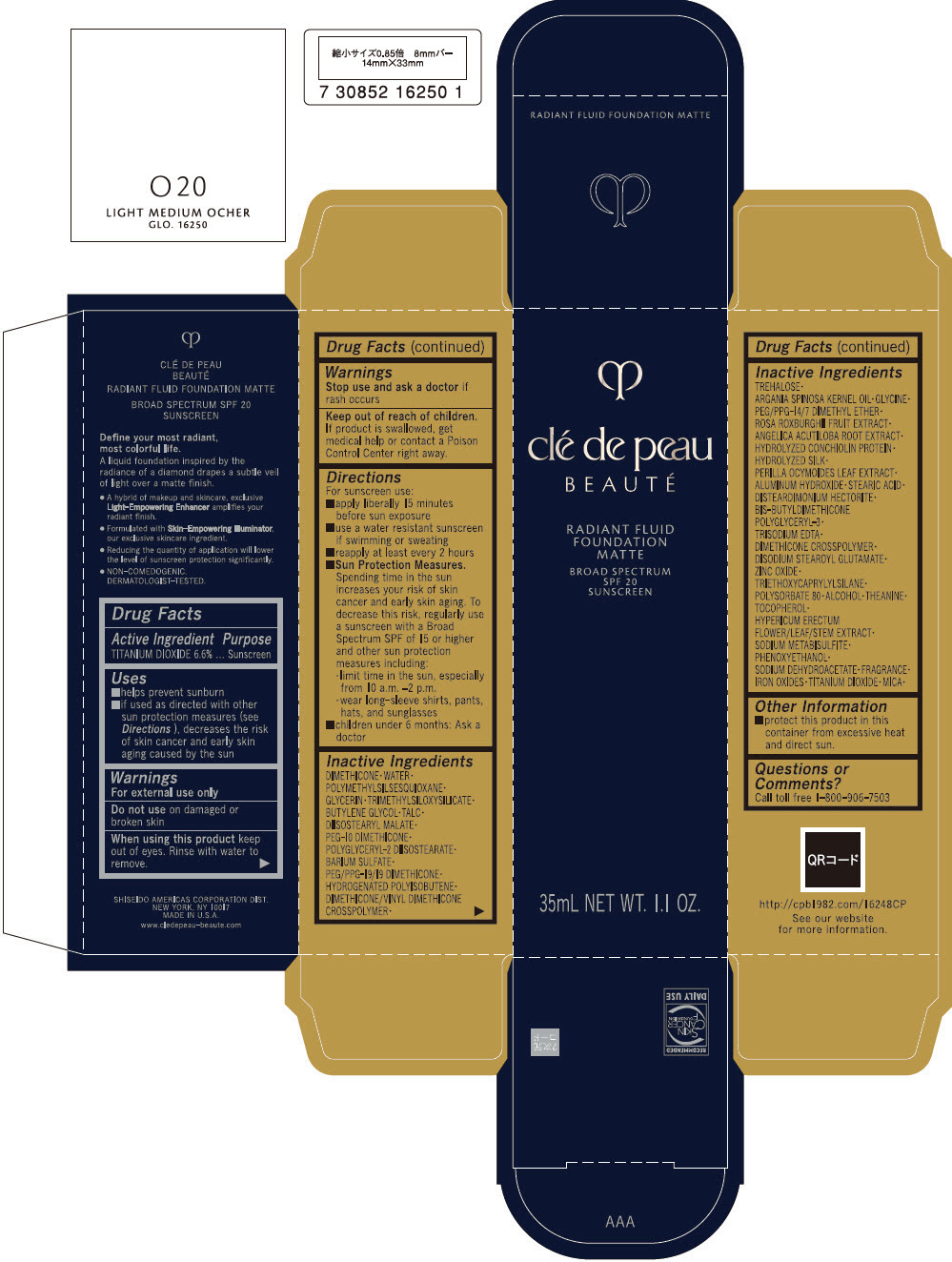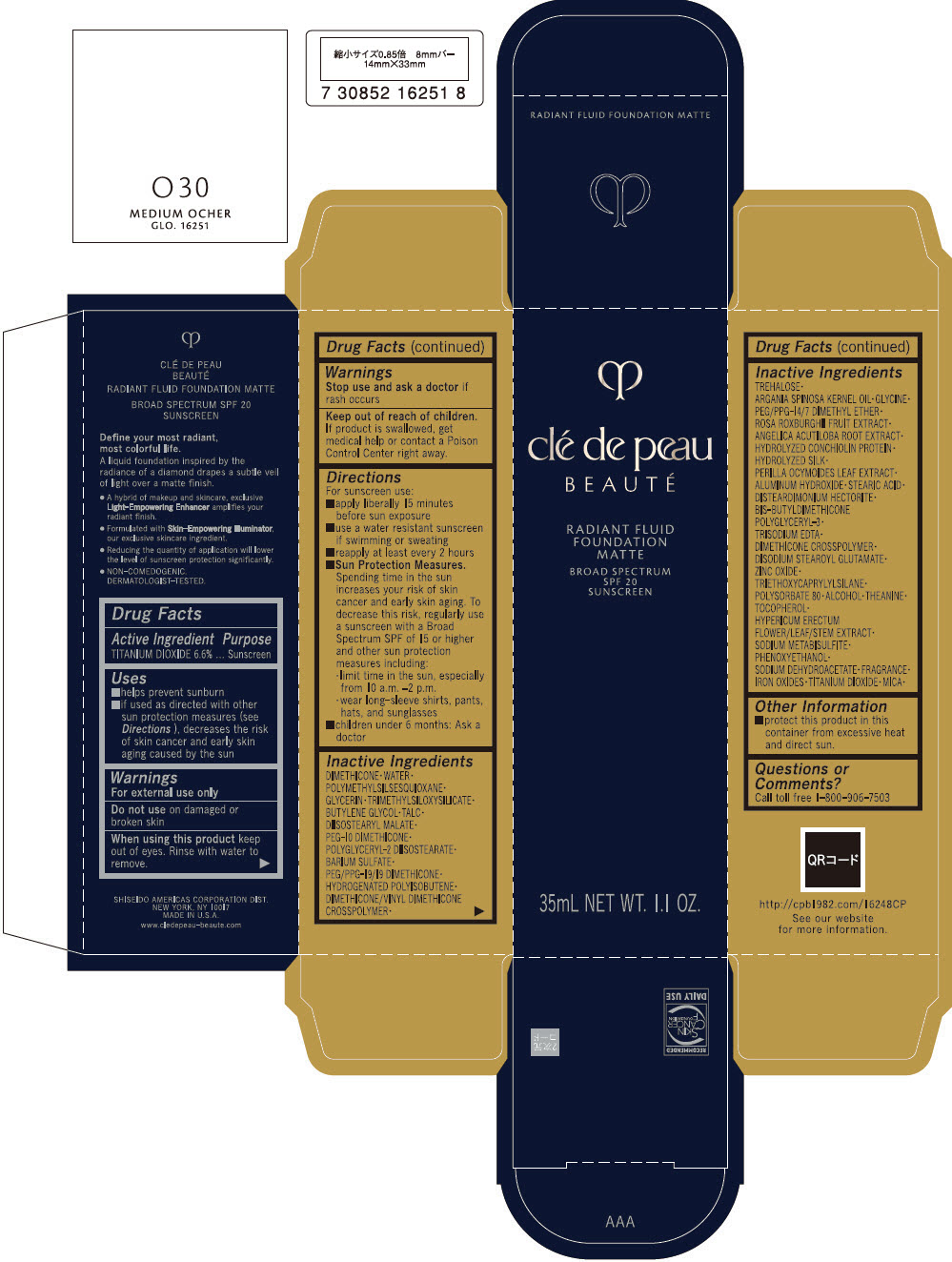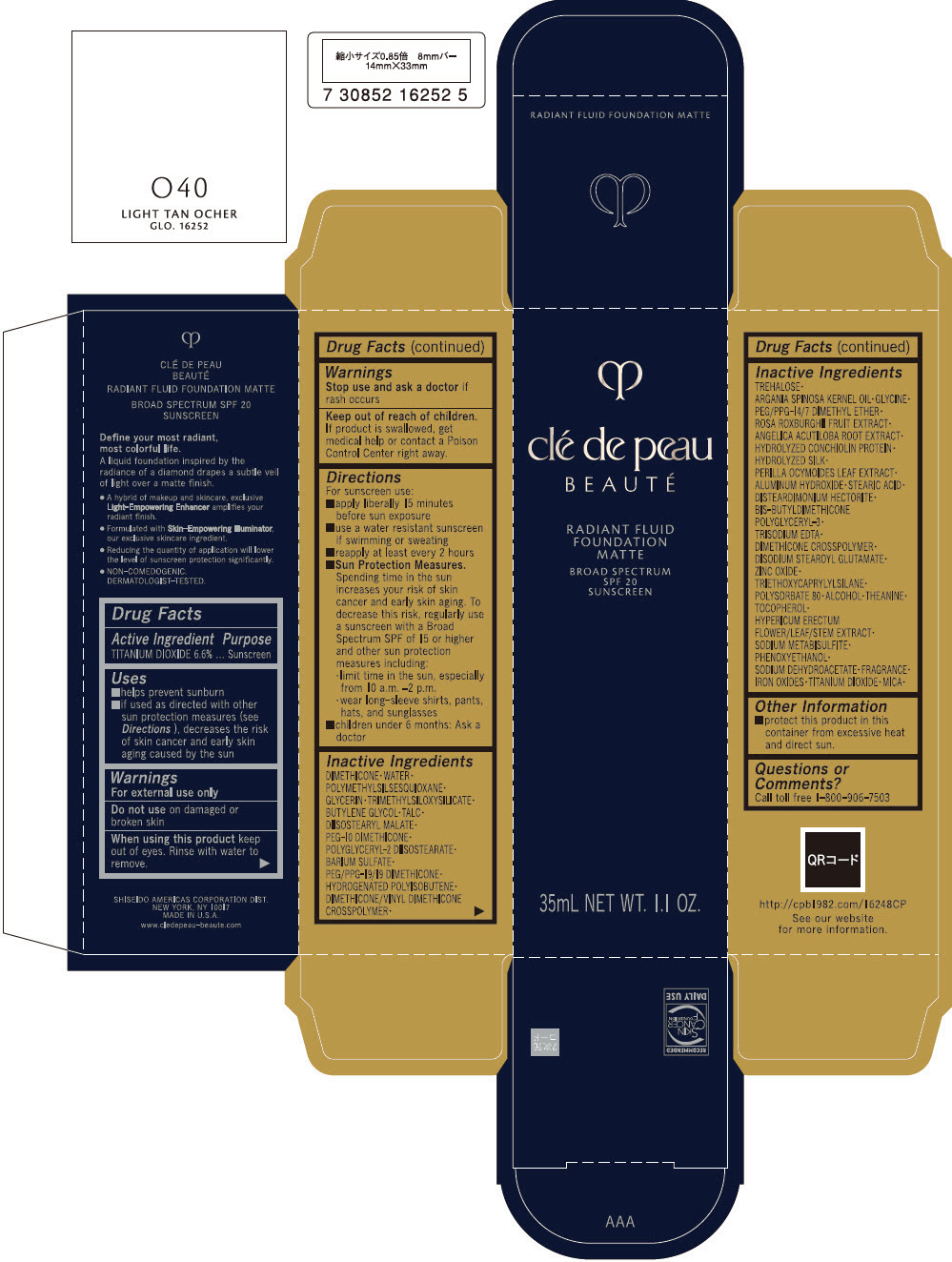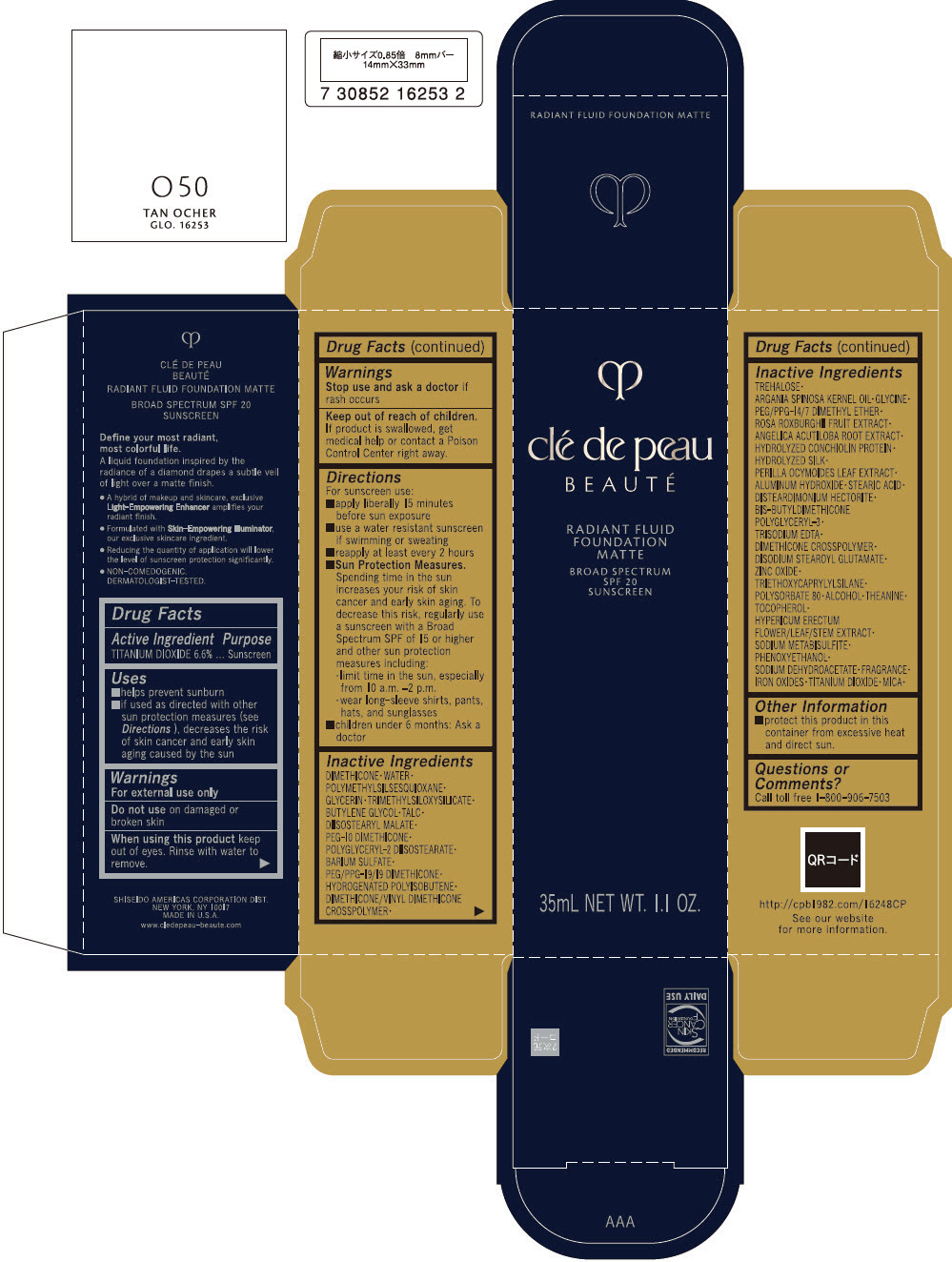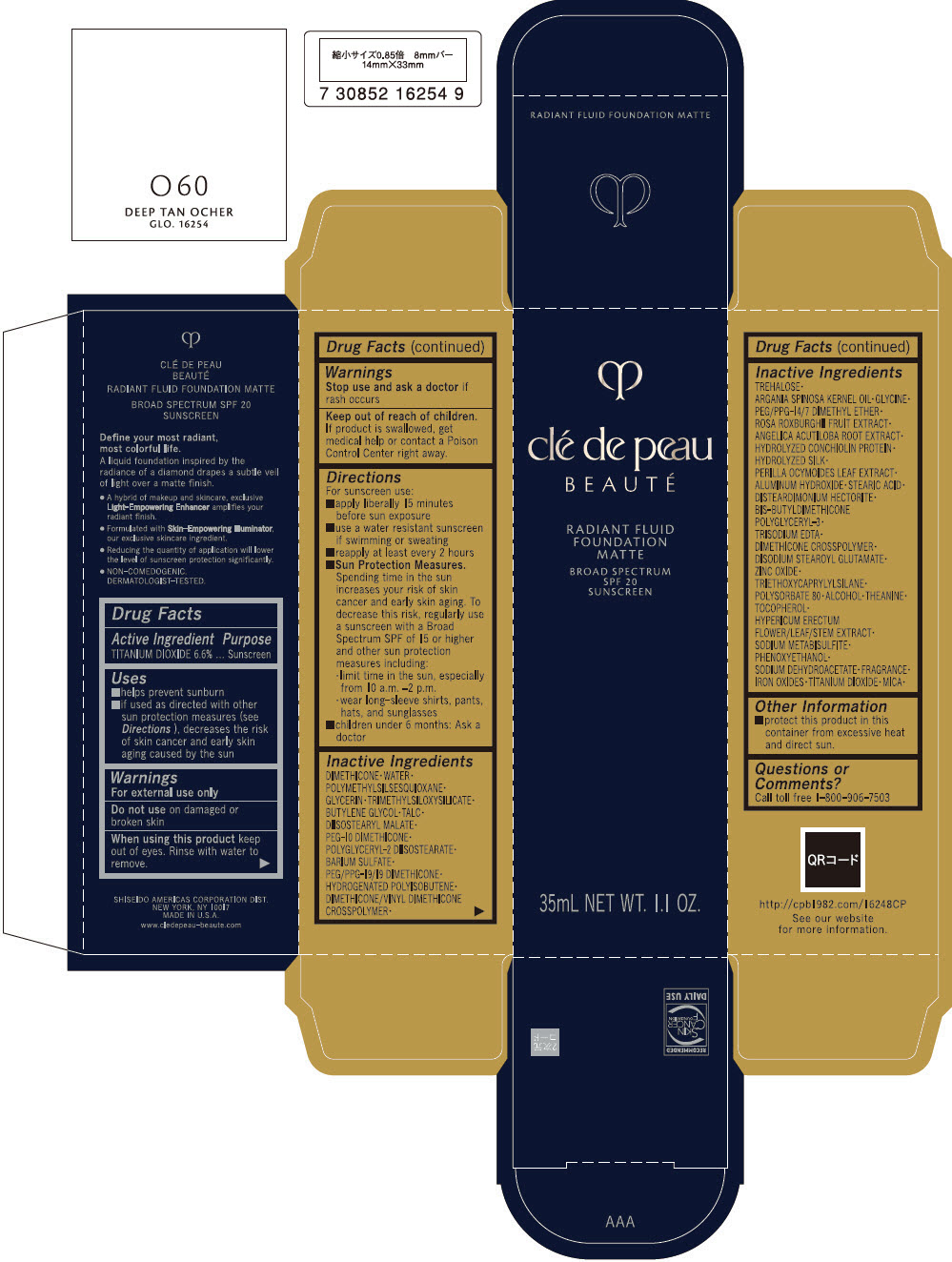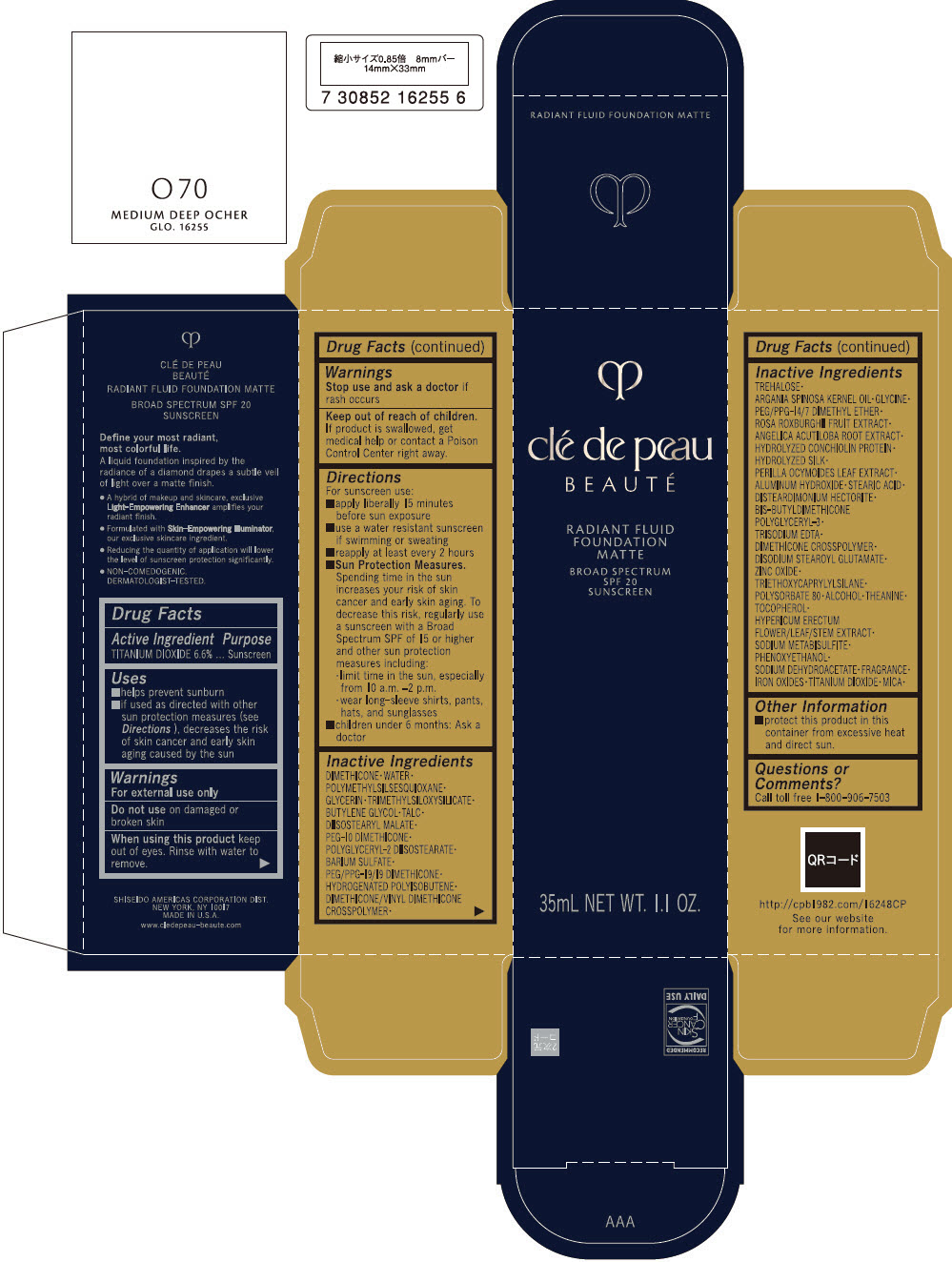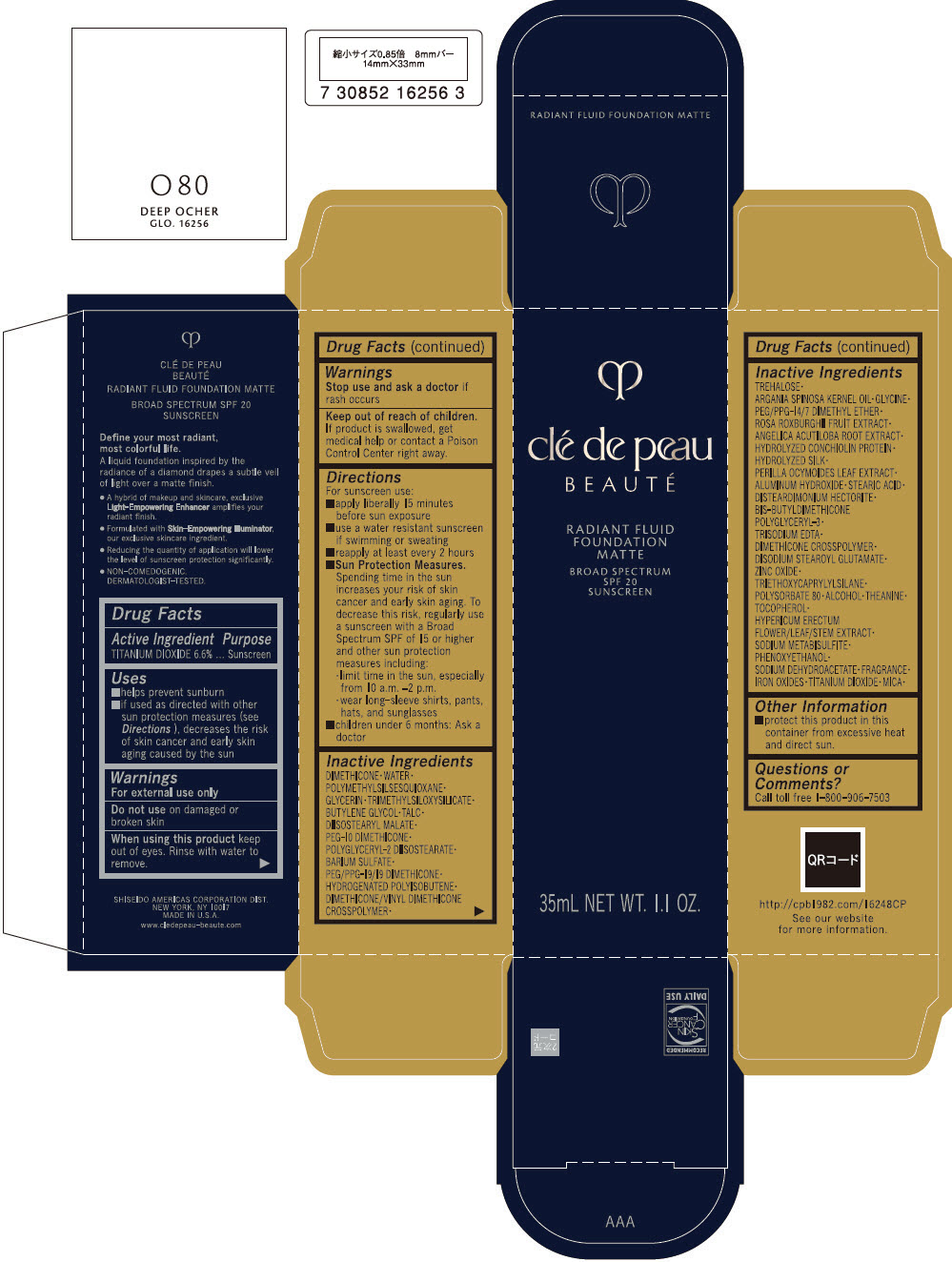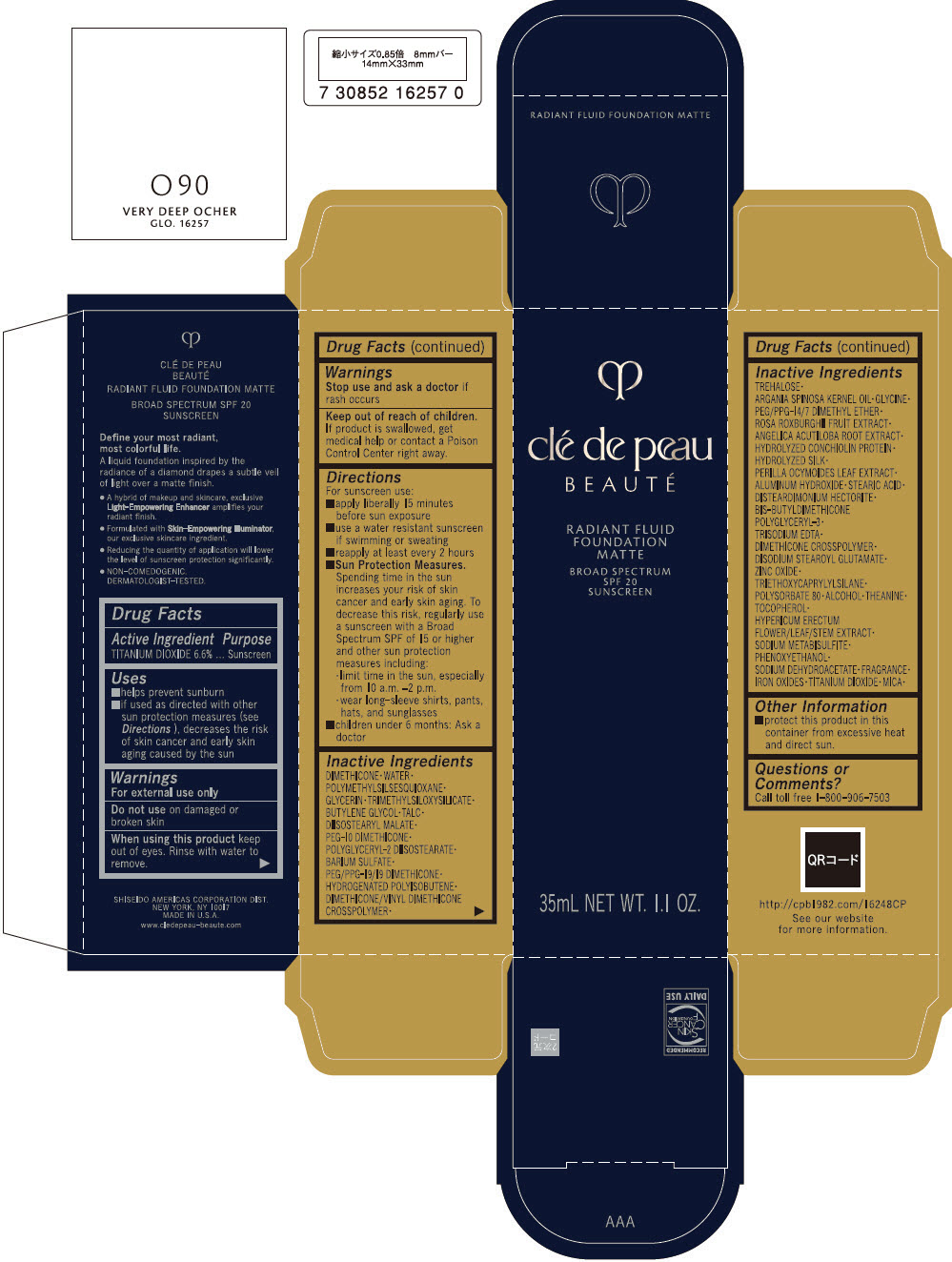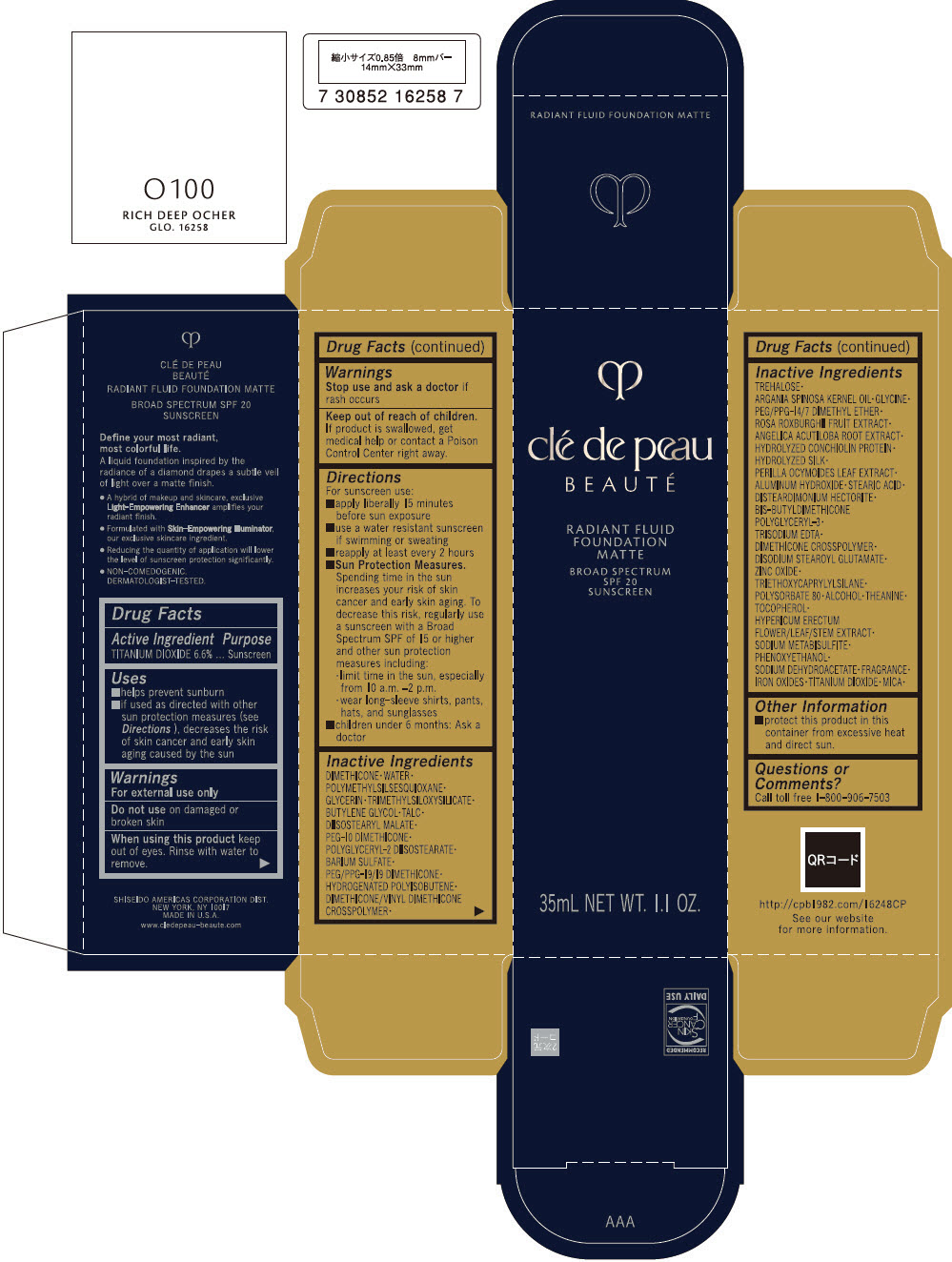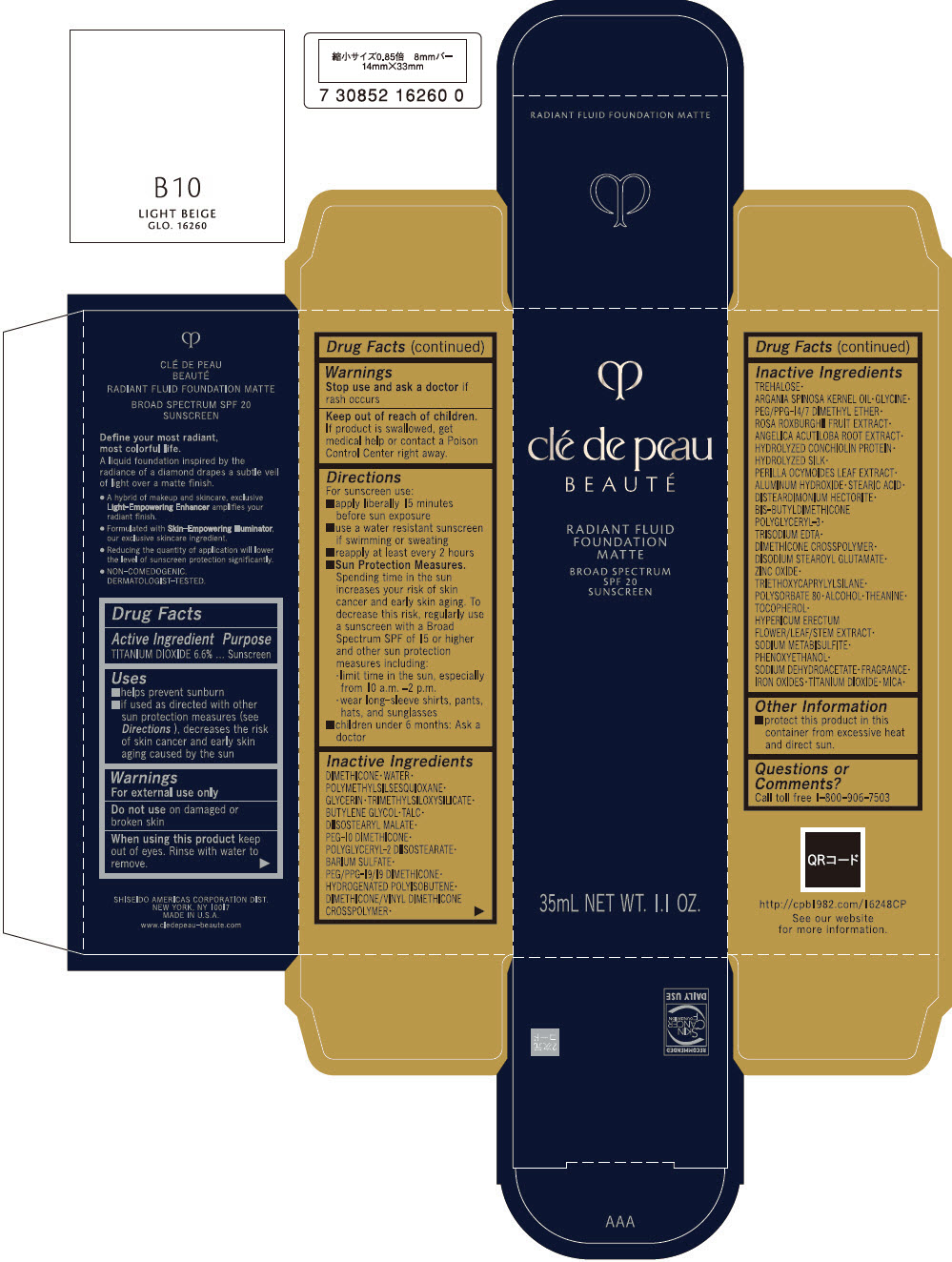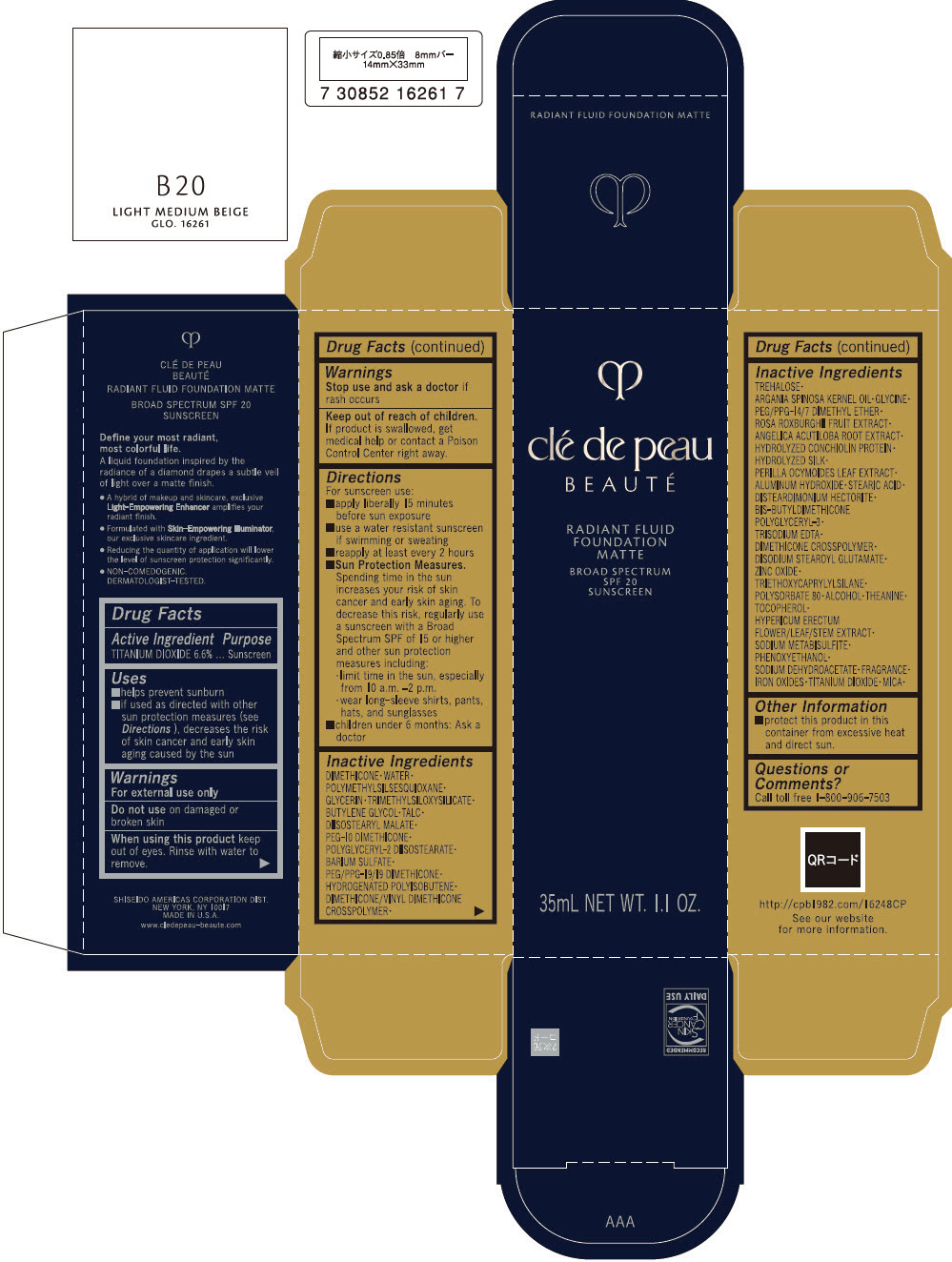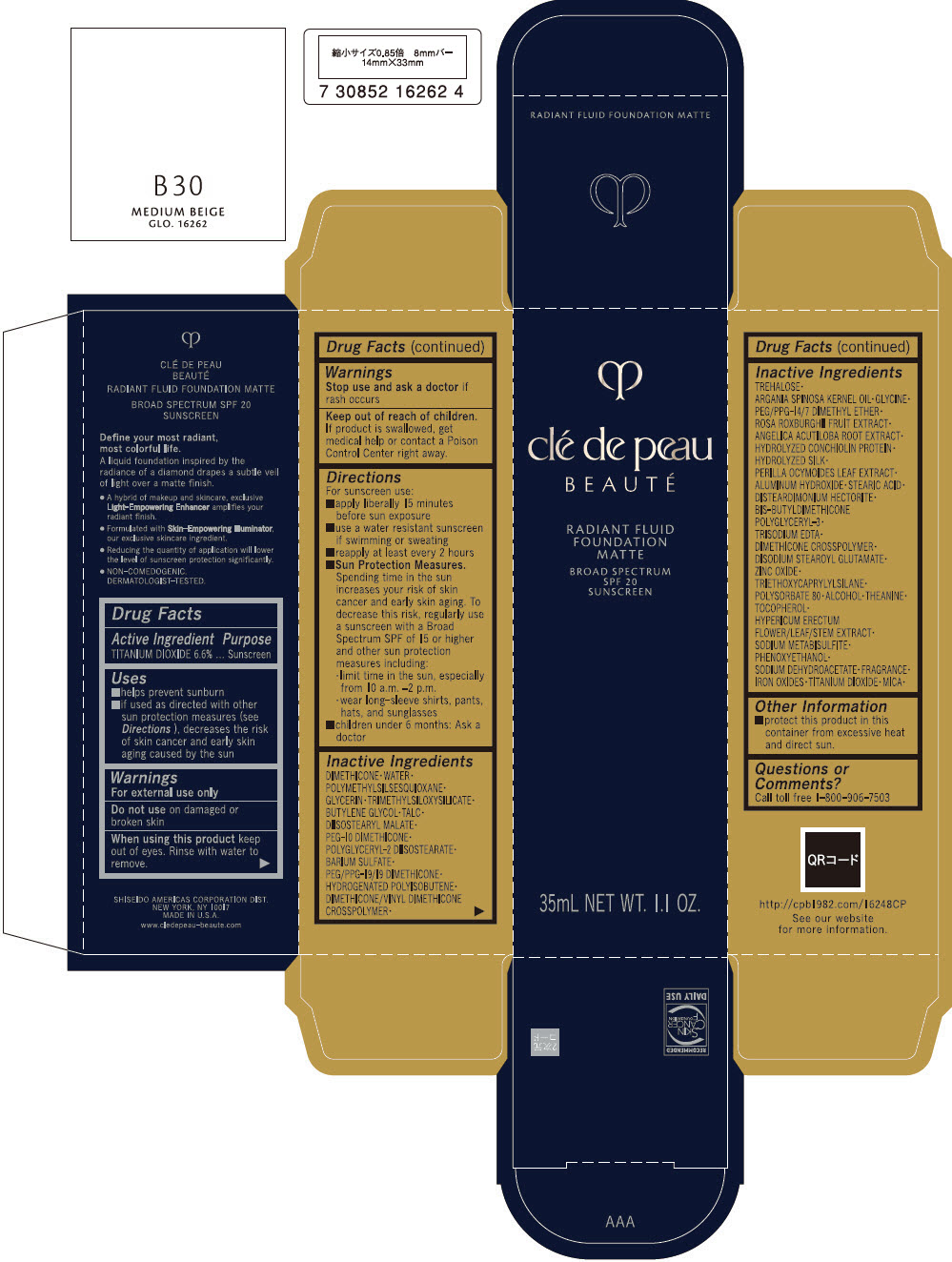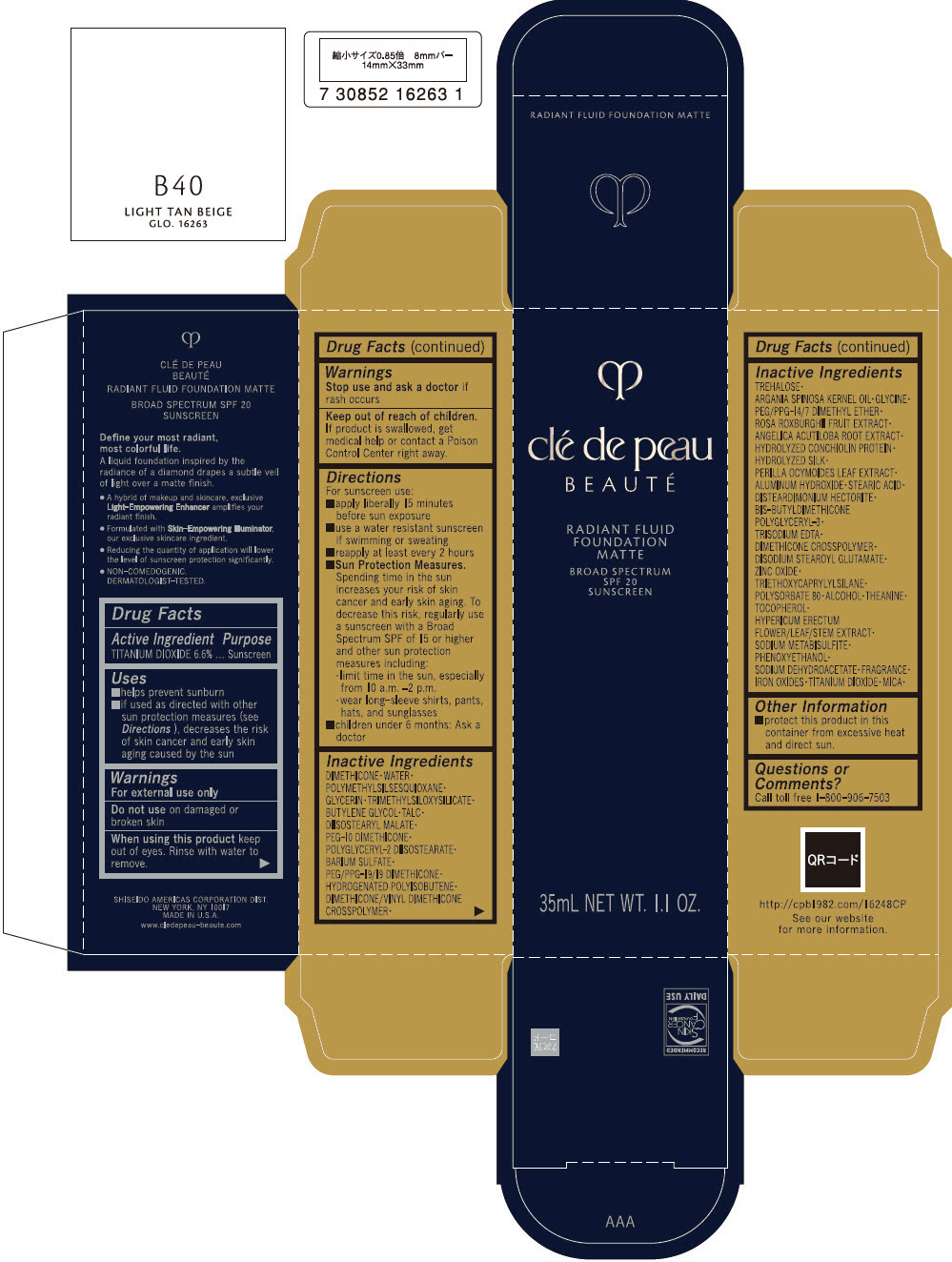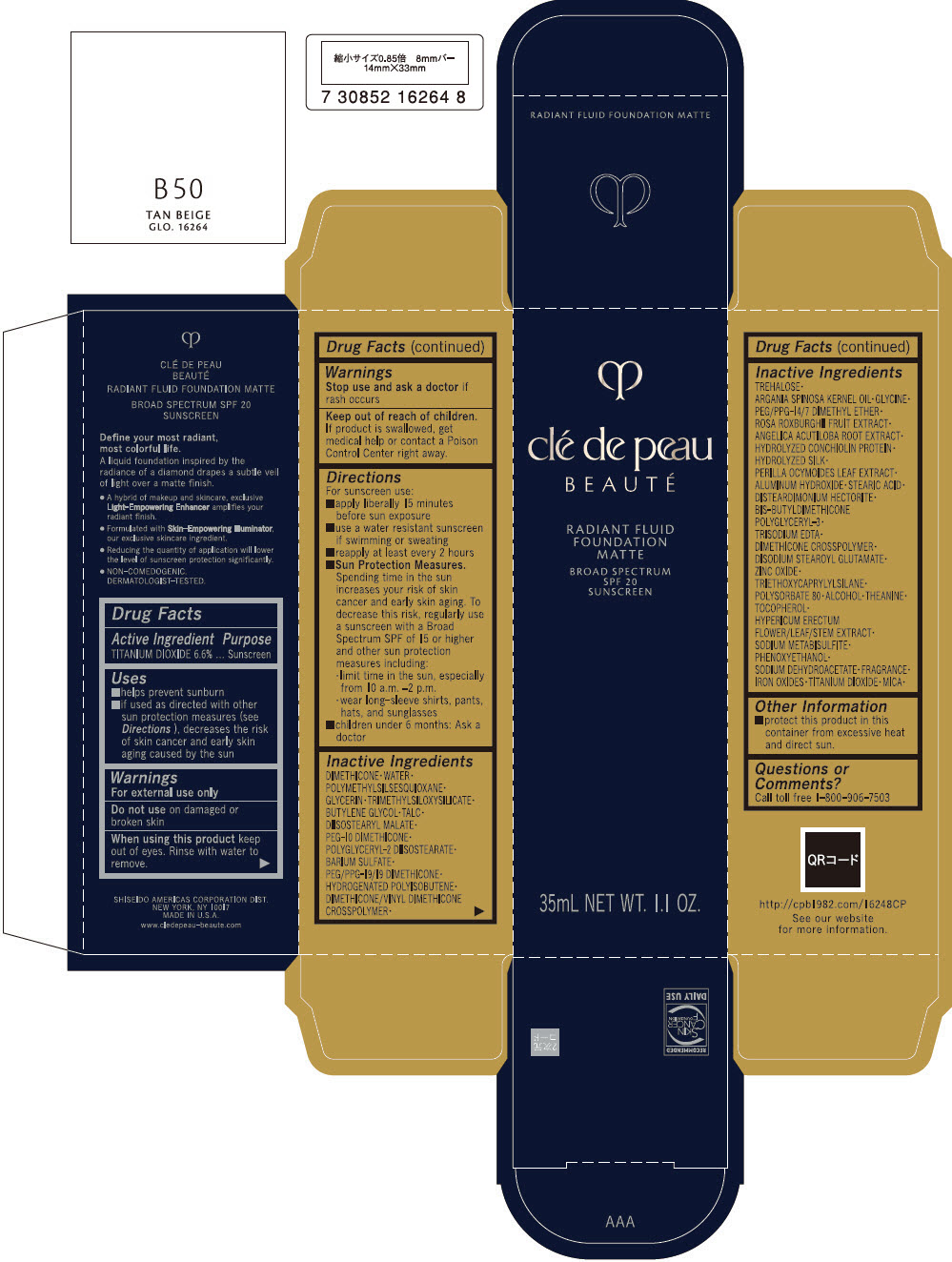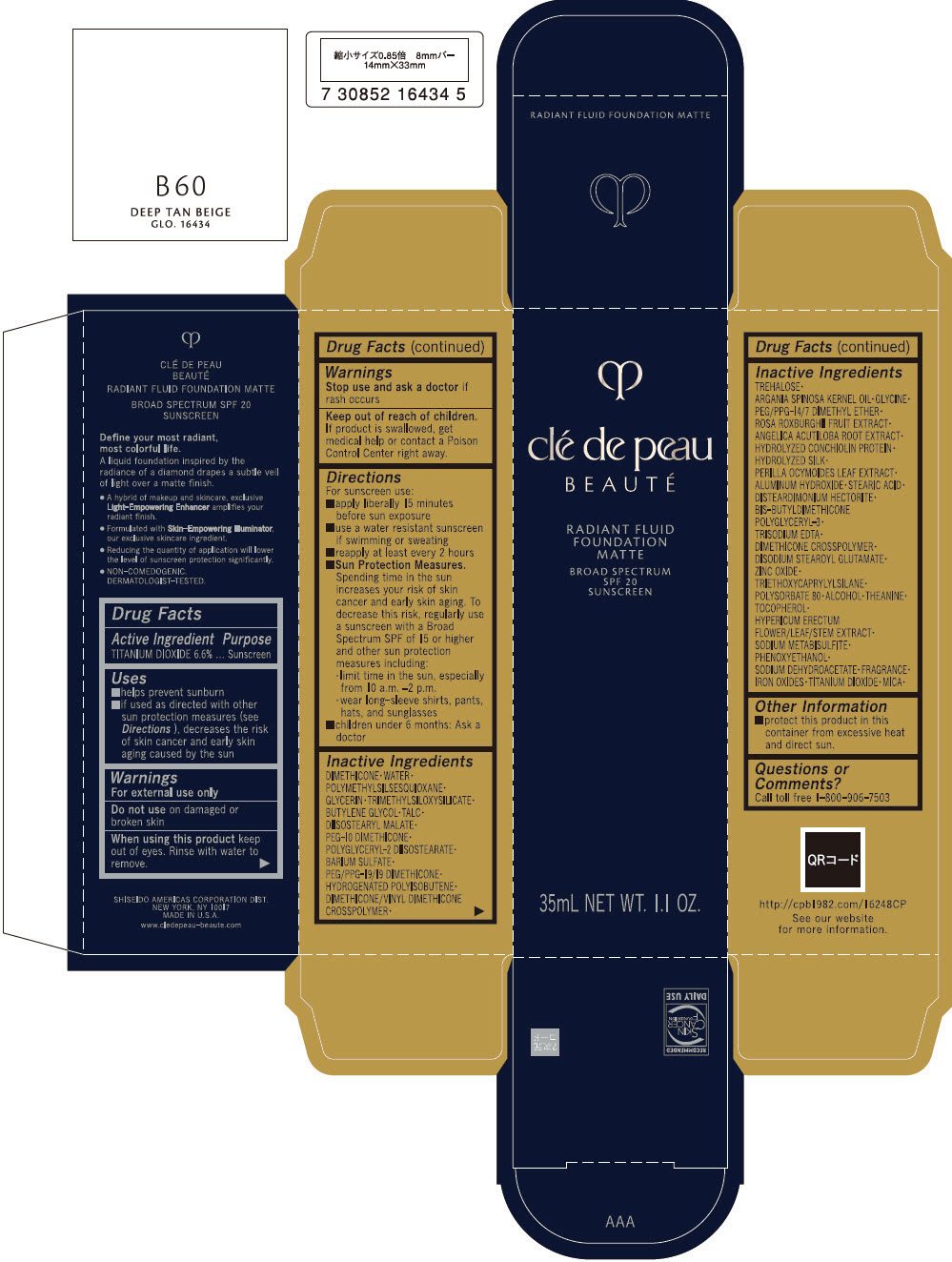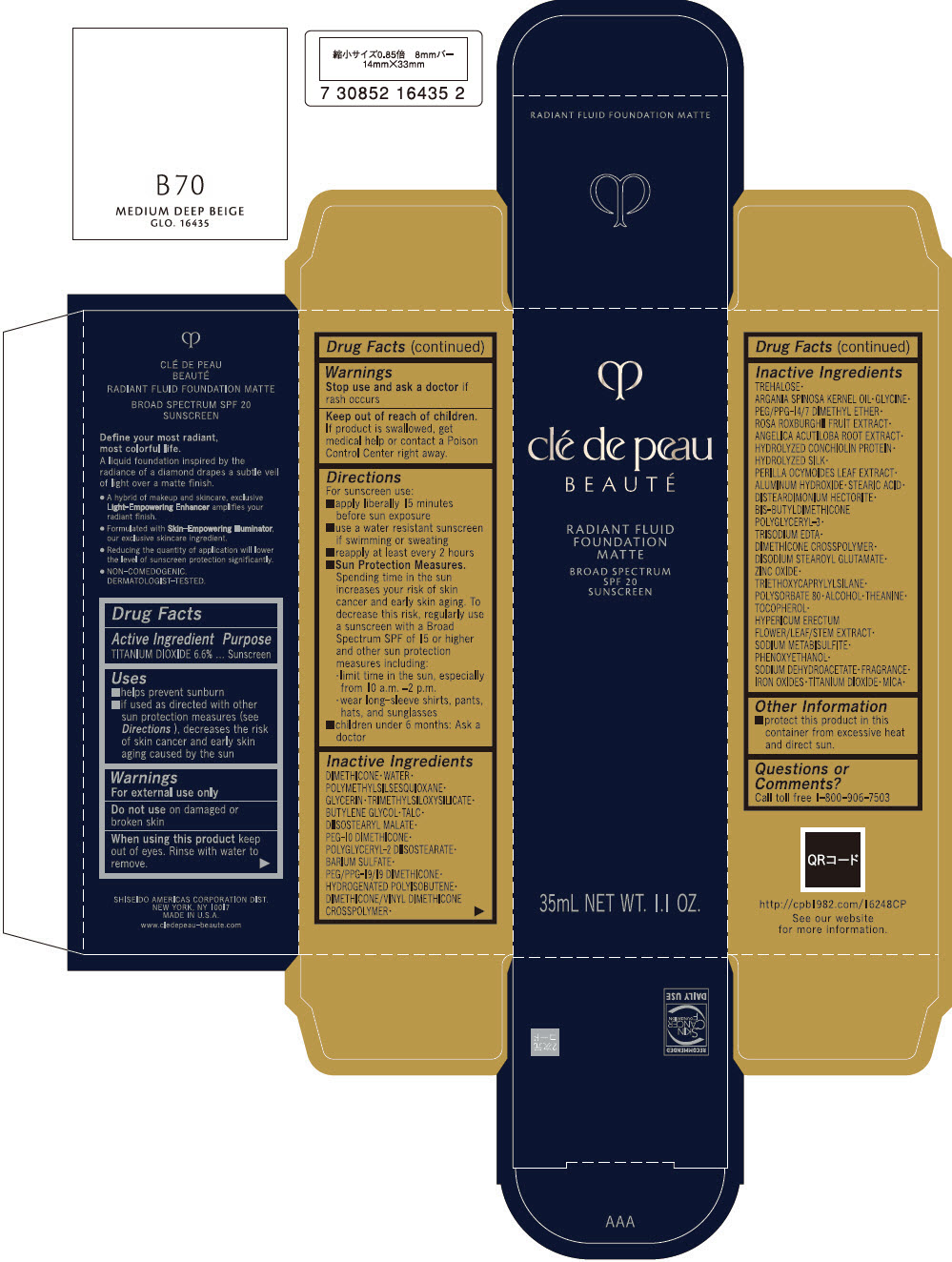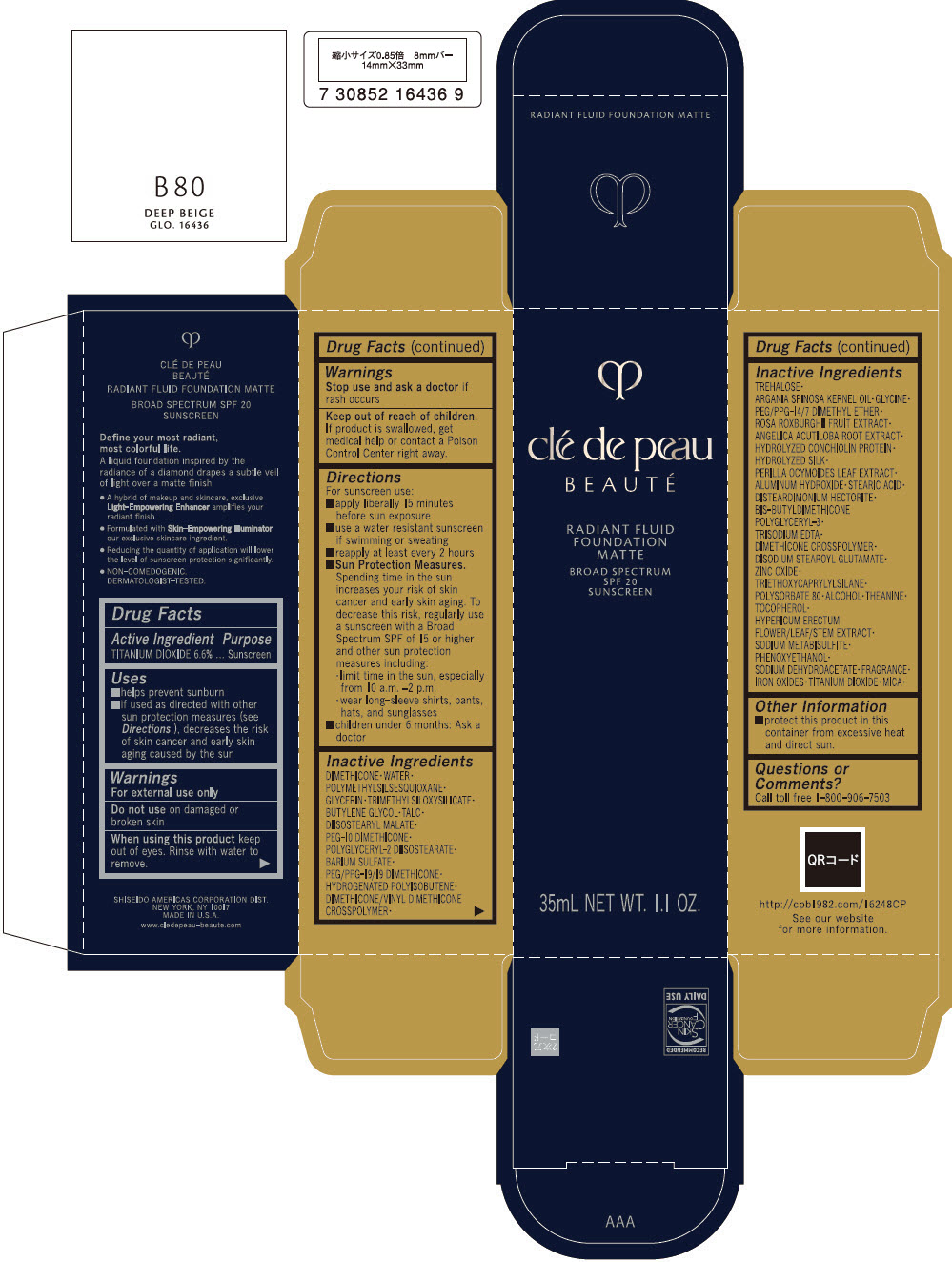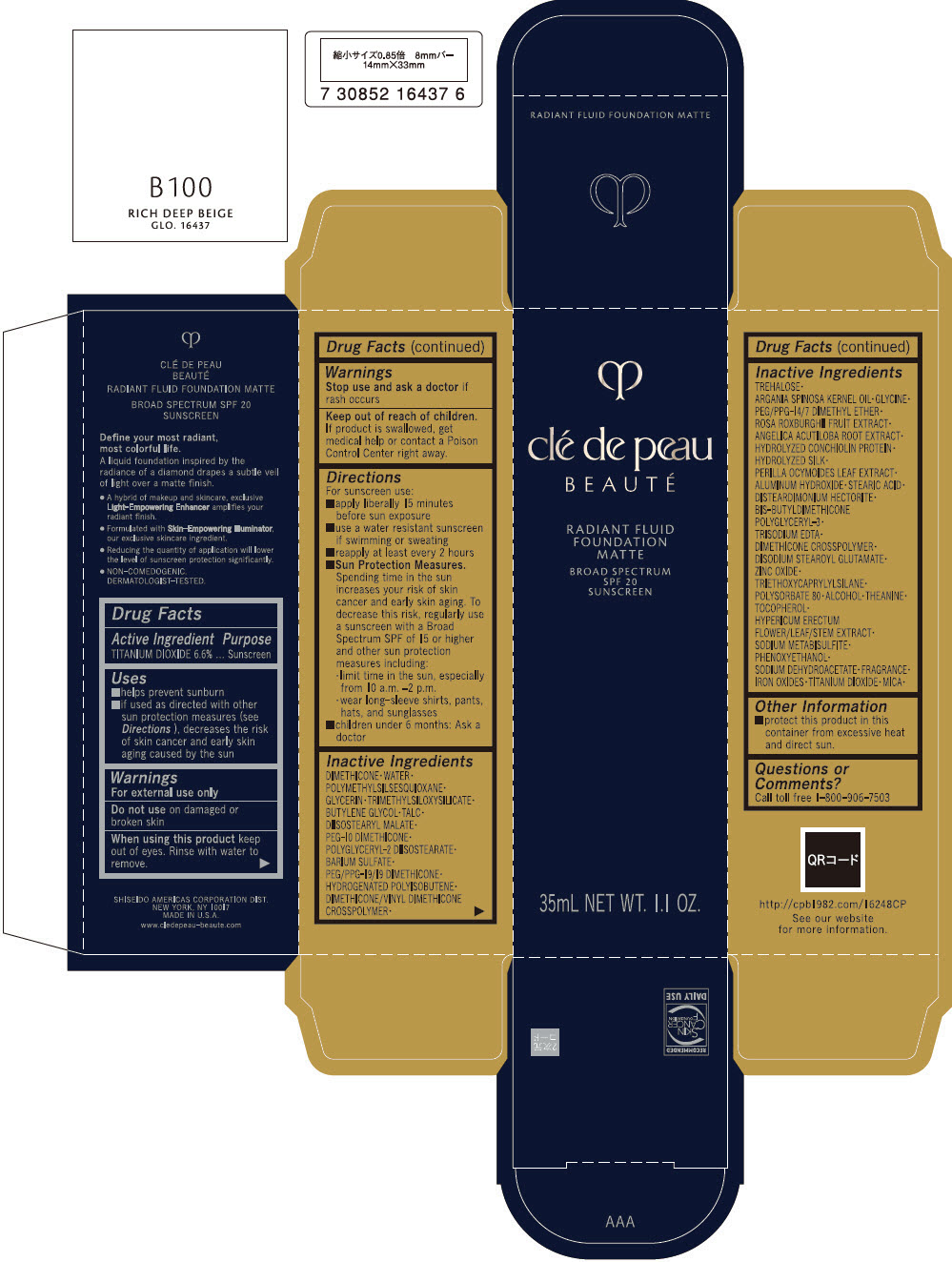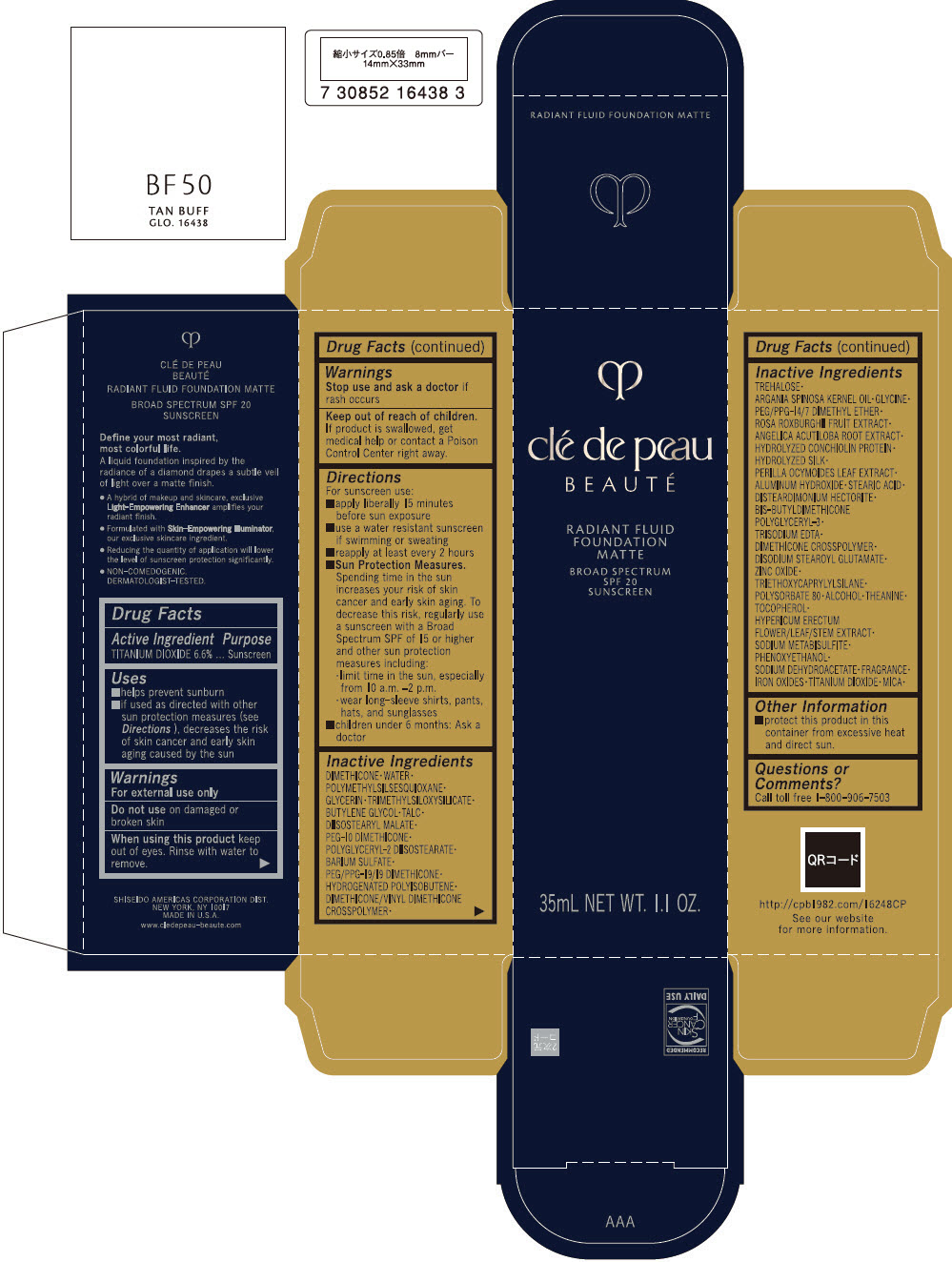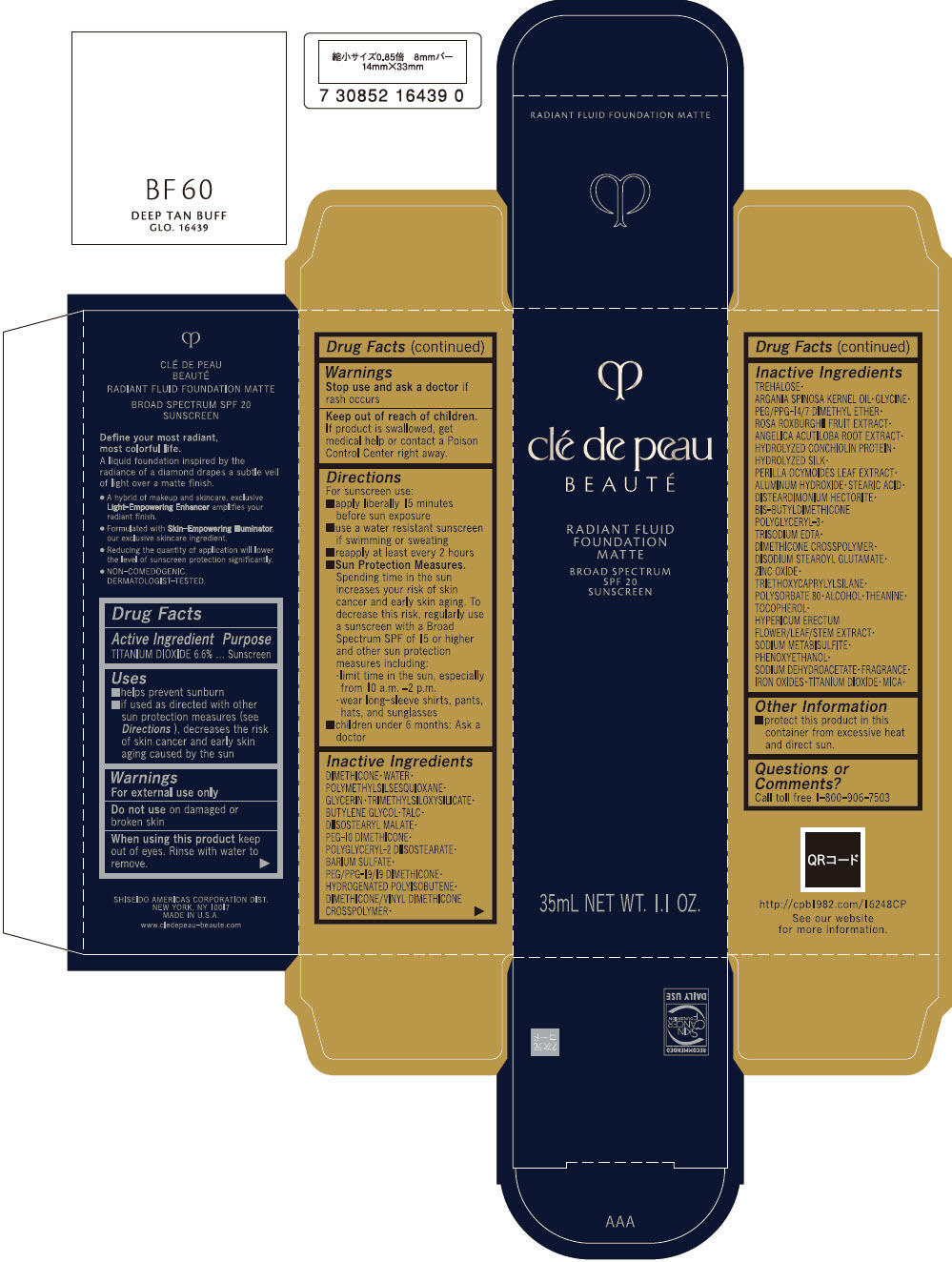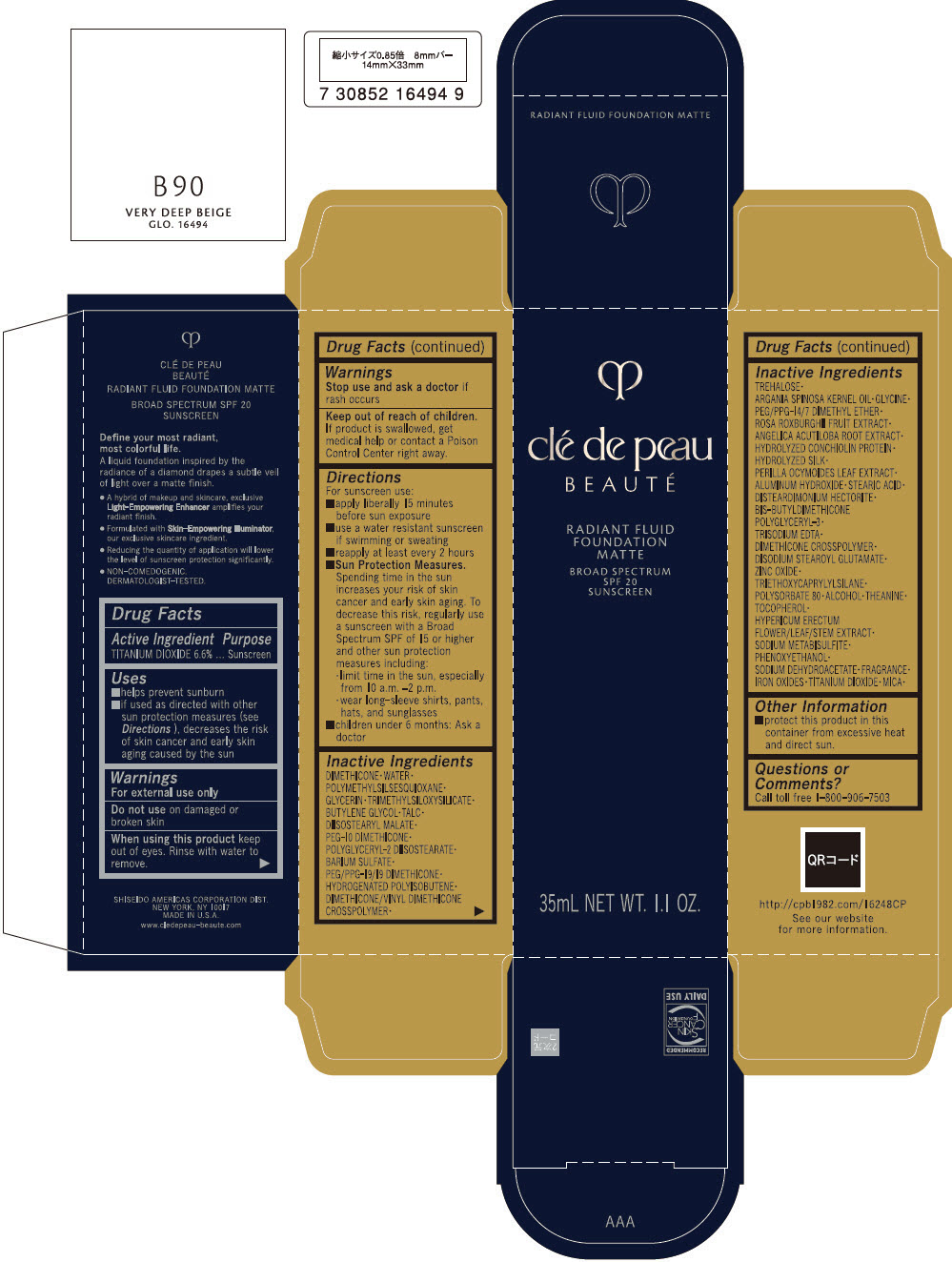 DRUG LABEL: cle de peau BEAUTE RADIANT FLUID FOUNDATION 

NDC: 58411-546 | Form: EMULSION
Manufacturer: SHISEIDO AMERICAS CORPORATION
Category: otc | Type: HUMAN OTC DRUG LABEL
Date: 20260105

ACTIVE INGREDIENTS: TITANIUM DIOXIDE 2.72118 g/35 mL
INACTIVE INGREDIENTS: DIMETHICONE; WATER; POLYMETHYLSILSESQUIOXANE (4.5 MICRONS); GLYCERIN; TRIMETHYLSILOXYSILICATE (M/Q 0.6-0.8); BUTYLENE GLYCOL; TALC; DIISOSTEARYL MALATE; PEG-10 DIMETHICONE (600 CST); POLYGLYCERYL-2 DIISOSTEARATE; BARIUM SULFATE; PEG/PPG-19/19 DIMETHICONE; HYDROGENATED POLYBUTENE (1300 MW); DIMETHICONE/VINYL DIMETHICONE CROSSPOLYMER (SOFT PARTICLE); TREHALOSE; ARGAN OIL; GLYCINE; PEG/PPG-14/7 DIMETHYL ETHER; ROSA ROXBURGHII FRUIT; ANGELICA ACUTILOBA ROOT; PERILLA FRUTESCENS LEAF; ALUMINUM HYDROXIDE; STEARIC ACID; DISTEARDIMONIUM HECTORITE; EDETATE TRISODIUM; DIMETHICONE CROSSPOLYMER (450000 MPA.S AT 12% IN CYCLOPENTASILOXANE); DISODIUM STEAROYL GLUTAMATE; ZINC OXIDE; TRIETHOXYCAPRYLYLSILANE; POLYSORBATE 80; ALCOHOL; THEANINE; .ALPHA.-TOCOPHEROL; HYPERICUM ERECTUM FLOWERING TOP; SODIUM METABISULFITE; PHENOXYETHANOL; SODIUM DEHYDROACETATE; FERRIC OXIDE RED; FERRIC OXIDE YELLOW; FERROSOFERRIC OXIDE; MICA

clé de peau BEAUTÉ RADIANT FLUID FOUNDATION

Drug Facts

Active Ingredients

TITANIUM DIOXIDE 6.6%

Purpose

Sunscreen

Uses

- helps prevent sunburn
- if used as directed with other sun protection measures (see Directions), decreases the risk of skin cancer and early skin aging caused by the sun

Warnings

For external use only

Do not use on damaged or broken skin

WHEN USING

When using this productkeep out of eyes. Rinse with water to remove.

Stop use and ask a doctorif rash occurs.

Keep out of reach of children.If product is swallowed, get medical help or contact a Poison Control Center right away.

Directions

For sunscreen use:

- apply liberally 15 minutes before sun exposure
- use a water resistant sunscreen if swimming or sweating
- reply at least every 2 hours
- Sun Protection Measures. Spending time in the sun increases your risk of skin cancer and early skin aging. To decrease this risk, regularly use a sunscreen with a Broad Spectrum SPF of 15 or higher and other un protection measures including:
  - limit time in the sun, especially from 10 a.m. – 2 p.m.
  - wear long-sleeve shirts, pants, hats, and sunglasses
- children under 6 months: Ask a doctor

Inactive Ingredients

DIMETHICONE ∙ WATER ∙ POLYMETHYLSILSESQUIOXANE ∙ GLYCERIN ∙ TRIMETHYLSILOXYSILICATE ∙ BUTYLENE GLYCOL ∙ TALC ∙ DIISOSTEARYL MALATE ∙ PEG-10 DIMETHICONE ∙ POLYGLYCERYL-2 DIISOSTEARATE ∙ BARIUM SULFATE ∙ PEG/PPG-19/19 DIMETHICONE ∙ HYDROGENATED POLYISOBUTENE ∙ DIMETHICONE/VINYL DIMETHICONE CROSSPOLYMER ∙ TREHALOSE ∙ ARGANIA SPINOSA KERNEL OIL ∙ GLYCINE ∙ PEG/PPG-14/7 DIMETHYL ETHER ∙ ROSA ROXBURGHII FRUIT EXTRACT ∙ ANGELICA ACUTILOBA ROOT EXTRACT ∙ HYDROLYZED CONCHIOLIN PROTEIN ∙ HYDROLYZED SILK ∙ PERILLA OCYMOIDES LEAF EXTRACT ∙ ALUMINUM HYDROXIDE ∙ STEARIC ACID ∙ DISTEARDIMONIUM HECTORITE ∙ BIS-BUTYLDIMETHICONE POLYGLYCERYL-3 ∙ TRISODIUM EDTA ∙ DIMETHICONE CROSSPOLYMER ∙ DISODIUM STEAROYL GLUTAMATE ∙ ZINC OXIDE ∙ TRIETHOXYCAPRYLYLSILANE ∙ POLYSORBATE 80 ∙ ALCOHOL ∙ THEANINE ∙ TOCOPHEROL ∙ HYPERICUM ERECTUM FLOWER/LEAF/STEM EXTRACT ∙ SODIUM METABISULFITE ∙ PHENOXYETHANOL ∙ SODIUM DEHYDROACETATE ∙ FRAGRANCE ∙ IRON OXIDES ∙ TITANIUM DIOXIDE ∙ MICA ∙

Other information

- protect this product in this container from excessive heat and direct sun.

Questions or comments?

Call toll free 1-800-906-7503

PRINCIPAL DISPLAY PANEL - 35 mL Bottle Carton - BF10 - LIGHT BUFF

clé de peau
BEAUTÉ

RADIANT FLUID
FOUNDATION
MATTE

BROAD SPECTRUM
SPF 20
SUNSCREEN

35mL NET WT. 1.1 OZ.

PRINCIPAL DISPLAY PANEL - 35 mL Bottle Carton - I10 - VERY LIGHT IVORY

clé de peau
BEAUTÉ

RADIANT FLUID
FOUNDATION
MATTE

BROAD SPECTRUM
SPF 20
SUNSCREEN

35mL NET WT. 1.1 OZ.

PRINCIPAL DISPLAY PANEL - 35 mL Bottle Carton - O10 - LIGHT OCHER

clé de peau
BEAUTÉ

RADIANT FLUID
FOUNDATION
MATTE

BROAD SPECTRUM
SPF 20
SUNSCREEN

35mL NET WT. 1.1 OZ.

PRINCIPAL DISPLAY PANEL - 35 mL Bottle Carton - O20 - LIGHT MEDIUM OCHER

clé de peau
BEAUTÉ

RADIANT FLUID
FOUNDATION
MATTE

BROAD SPECTRUM
SPF 20
SUNSCREEN

35mL NET WT. 1.1 OZ.

PRINCIPAL DISPLAY PANEL - 35 mL Bottle Carton - O30 - MEDIUM OCHER

clé de peau
BEAUTÉ

RADIANT FLUID
FOUNDATION
MATTE

BROAD SPECTRUM
SPF 20
SUNSCREEN

35mL NET WT. 1.1 OZ.

PRINCIPAL DISPLAY PANEL - 35 mL Bottle Carton - O40 - LIGHT TAN OCHER

clé de peau
BEAUTÉ

RADIANT FLUID
FOUNDATION
MATTE

BROAD SPECTRUM
SPF 20
SUNSCREEN

35mL NET WT. 1.1 OZ.

PRINCIPAL DISPLAY PANEL - 35 mL Bottle Carton - O50 - TAN OCHER

clé de peau
BEAUTÉ

RADIANT FLUID
FOUNDATION
MATTE

BROAD SPECTRUM
SPF 20
SUNSCREEN

35mL NET WT. 1.1 OZ.

PRINCIPAL DISPLAY PANEL - 35 mL Bottle Carton - O60 - DEEP TAN OCHER

clé de peau
BEAUTÉ

RADIANT FLUID
FOUNDATION
MATTE

BROAD SPECTRUM
SPF 20
SUNSCREEN

35mL NET WT. 1.1 OZ.

PRINCIPAL DISPLAY PANEL - 35 mL Bottle Carton - O70 - MEDIUM DEEP OCHER

clé de peau
BEAUTÉ

RADIANT FLUID
FOUNDATION
MATTE

BROAD SPECTRUM
SPF 20
SUNSCREEN

35mL NET WT. 1.1 OZ.

PRINCIPAL DISPLAY PANEL - 35 mL Bottle Carton - O80 - DEEP OCHER

clé de peau
BEAUTÉ

RADIANT FLUID
FOUNDATION
MATTE

BROAD SPECTRUM
SPF 20
SUNSCREEN

35mL NET WT. 1.1 OZ.

PRINCIPAL DISPLAY PANEL - 35 mL Bottle Carton - O90 - VERY DEEP OCHER

clé de peau
BEAUTÉ

RADIANT FLUID
FOUNDATION
MATTE

BROAD SPECTRUM
SPF 20
SUNSCREEN

35mL NET WT. 1.1 OZ.

PRINCIPAL DISPLAY PANEL - 35 mL Bottle Carton - O100 - RICH DEEP OCHER

clé de peau
BEAUTÉ

RADIANT FLUID
FOUNDATION
MATTE

BROAD SPECTRUM
SPF 20
SUNSCREEN

35mL NET WT. 1.1 OZ.

PRINCIPAL DISPLAY PANEL - 35 mL Bottle Carton - B10 - LIGHT BEIGE

clé de peau
BEAUTÉ

RADIANT FLUID
FOUNDATION
MATTE

BROAD SPECTRUM
SPF 20
SUNSCREEN

35mL NET WT. 1.1 OZ.

PRINCIPAL DISPLAY PANEL - 35 mL Bottle Carton - B20 - LIGHT MEDIUM BEIGE

clé de peau
BEAUTÉ

RADIANT FLUID
FOUNDATION
MATTE

BROAD SPECTRUM
SPF 20
SUNSCREEN

35mL NET WT. 1.1 OZ.

PRINCIPAL DISPLAY PANEL - 35 mL Bottle Carton - B30 - MEDIUM BEIGE

clé de peau
BEAUTÉ

RADIANT FLUID
FOUNDATION
MATTE

BROAD SPECTRUM
SPF 20
SUNSCREEN

35mL NET WT. 1.1 OZ.

PRINCIPAL DISPLAY PANEL - 35 mL Bottle Carton - B40 - LIGHT TAN BEIGE

clé de peau
BEAUTÉ

RADIANT FLUID
FOUNDATION
MATTE

BROAD SPECTRUM
SPF 20
SUNSCREEN

35mL NET WT. 1.1 OZ.

PRINCIPAL DISPLAY PANEL - 35 mL Bottle Carton - B50 - TAN BEIGE

clé de peau
BEAUTÉ

RADIANT FLUID
FOUNDATION
MATTE

BROAD SPECTRUM
SPF 20
SUNSCREEN

35mL NET WT. 1.1 OZ.

PRINCIPAL DISPLAY PANEL - 35 mL Bottle Carton - B60 - DEEP TAN BEIGE

clé de peau
BEAUTÉ

RADIANT FLUID
FOUNDATION
MATTE

BROAD SPECTRUM
SPF 20
SUNSCREEN

35mL NET WT. 1.1 OZ.

PRINCIPAL DISPLAY PANEL - 35 mL Bottle Carton - B70 - MEDIUM DEEP BEIGE

clé de peau
BEAUTÉ

RADIANT FLUID
FOUNDATION
MATTE

BROAD SPECTRUM
SPF 20
SUNSCREEN

35mL NET WT. 1.1 OZ.

PRINCIPAL DISPLAY PANEL - 35 mL Bottle Carton - B80 - DEEP BEIGE

clé de peau
BEAUTÉ

RADIANT FLUID
FOUNDATION
MATTE

BROAD SPECTRUM
SPF 20
SUNSCREEN

35mL NET WT. 1.1 OZ.

PRINCIPAL DISPLAY PANEL - 35 mL Bottle Carton - B100 - RICH DEEP BEIGE

clé de peau
BEAUTÉ

RADIANT FLUID
FOUNDATION
MATTE

BROAD SPECTRUM
SPF 20
SUNSCREEN

35mL NET WT. 1.1 OZ.

PRINCIPAL DISPLAY PANEL - 35 mL Bottle Carton - BF50 - TAN BUFF

clé de peau
BEAUTÉ

RADIANT FLUID
FOUNDATION
MATTE

BROAD SPECTRUM
SPF 20
SUNSCREEN

35mL NET WT. 1.1 OZ.

PRINCIPAL DISPLAY PANEL - 35 mL Bottle Carton - BF60 - DEEP TAN BUFF

clé de peau
BEAUTÉ

RADIANT FLUID
FOUNDATION
MATTE

BROAD SPECTRUM
SPF 20
SUNSCREEN

35mL NET WT. 1.1 OZ.

PRINCIPAL DISPLAY PANEL - 35 mL Bottle Carton - B90 - VERY DEEP BEIGE

clé de peau
BEAUTÉ

RADIANT FLUID
FOUNDATION
MATTE

BROAD SPECTRUM
SPF 20
SUNSCREEN

35mL NET WT. 1.1 OZ.